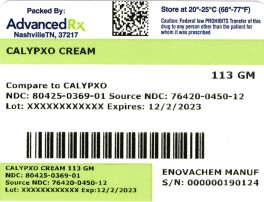 DRUG LABEL: Calypxo Pain Relief
NDC: 80425-0369 | Form: CREAM
Manufacturer: Advanced Rx of Tennessee, LLC
Category: otc | Type: HUMAN OTC DRUG LABEL
Date: 20241231

ACTIVE INGREDIENTS: METHYL SALICYLATE 10 g/100 g; MENTHOL 3 g/100 g
INACTIVE INGREDIENTS: CARBOMER INTERPOLYMER TYPE A (ALLYL SUCROSE CROSSLINKED); ALOE VERA LEAF; WATER; CETYL ALCOHOL; DIAZOLIDINYL UREA; ISOPROPYL MYRISTATE; METHYLPARABEN; POLYETHYLENE GLYCOL 400; PROPYLPARABEN; PROPYLENE GLYCOL; SODIUM LAURYL SULFATE; TROLAMINE

Calypxo Cream

Drugs Facts

Active Ingredients

Methyl Salicylate………10.00%

Menthol…………………3.00%

Purpose

Topical Analgesic

Topical Analgesic

Uses

For temporary relief of minor aches and pains associated with simple backaches, arthritis, bruises, sprains and cramps.

Warning

For external use only.

Avoid contact with eyes and mucous membranes.

Do not bandage tightly or cover treated areas.

Do not use with heating pad.

Do not apply to open wounds or damages skin.

A mild burning sensation may occur. If severe burning sensation occurs, discontinue use immediately.

If symptoms persist for more than seven days, discontinue use and consult physician.

Keep out of reach of children.If swallowed, consult physician.

If pregnant or breast feeding, contact physician prior to use.

Directions

For adults apply directly to affected area. Repeat as necessary, but do not use more than 3-4 times daily.

Additional Information

Store at room temperature.

Other Ingredients

Acrylates/C10-30 Alkyl Acrylate Crosspolymer, Aloe Barbadensis Leaf (Aloe Vera Gel) Juice, Aqua (Deionized Water), Cetyl Alcohol, Diazolidinyl Urea, Isopropyl Myristate, Methyl Paraben, PEG-8, Propyl Paraben, Propylene Glycol, Sodium lauryl Sulfate, Triethanolamine.